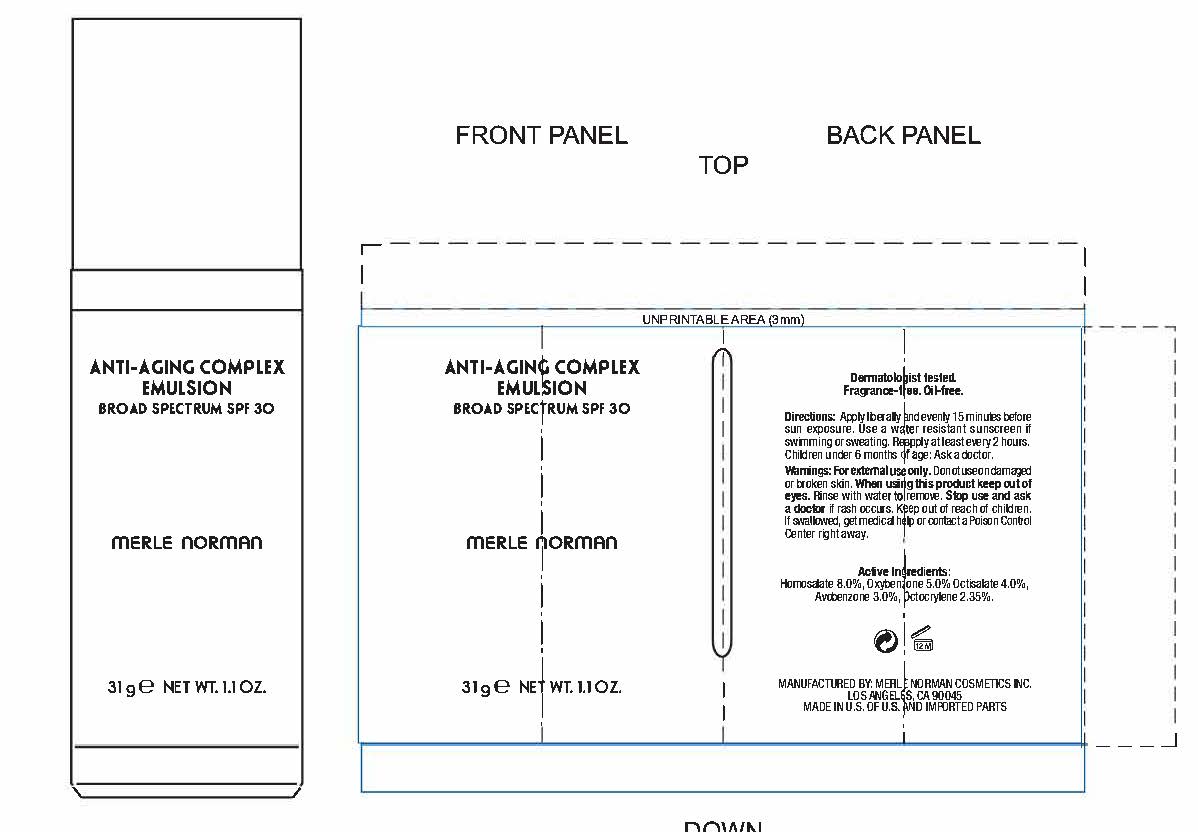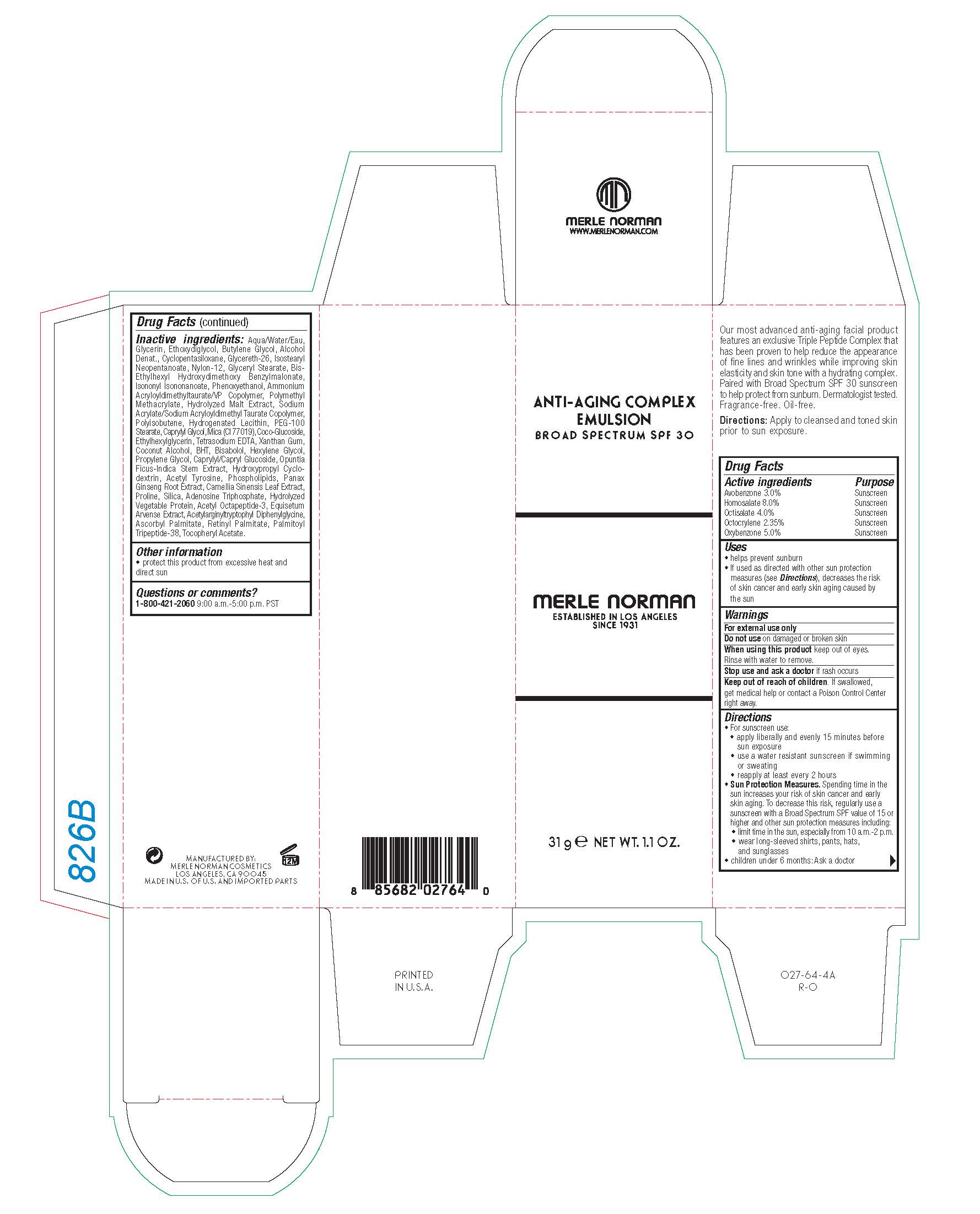 DRUG LABEL: ANTI-AGING COMPLEX BROAD SPECTRUM SPF 30
NDC: 57627-204 | Form: CREAM
Manufacturer: Merle Norman Cosmetics, Inc.
Category: otc | Type: HUMAN OTC DRUG LABEL
Date: 20251118

ACTIVE INGREDIENTS: OCTISALATE 4 g/100 g; OCTOCRYLENE 2.35 g/100 g; OXYBENZONE 5 g/100 g; AVOBENZONE 3 g/100 g; HOMOSALATE 8 g/100 g
INACTIVE INGREDIENTS: GLYCERYL MONOSTEARATE; BIS-ETHYLHEXYL HYDROXYDIMETHOXY BENZYLMALONATE; ISONONYL ISONONANOATE; MICA; EDETATE SODIUM; XANTHAN GUM; GREEN TEA LEAF; ASIAN GINSENG; AMMONIUM ACRYLOYLDIMETHYLTAURATE/VP COPOLYMER; WATER; BUTYLENE GLYCOL; CYCLOMETHICONE 5; GLYCERETH-26; PALMITOYL LYSYLDIOXYMETHIONYLLYSINE; ISOSTEARYL NEOPENTANOATE; NYLON-12; VITAMIN A PALMITATE; .ALPHA.-TOCOPHEROL ACETATE; EQUISETUM ARVENSE BRANCH; PHENOXYETHANOL; POLY(METHYL METHACRYLATE; 450000 MW); ACETYL OCTAPEPTIDE-3; PROLINE; ASCORBYL PALMITATE; DIETHYLENE GLYCOL MONOETHYL ETHER; ALCOHOL; PEG-100 STEARATE; ETHYLHEXYLGLYCERIN; COCONUT ALCOHOL; CAPRYLYL/CAPRYL OLIGOGLUCOSIDE; OPUNTIA FICUS-INDICA STEM; ACETYLARGINYLTRYPTOPHYL DIPHENYLGLYCINE; LECITHIN, SOYBEAN; HYDROGENATED SOYBEAN LECITHIN; CAPRYLYL GLYCOL; ACETYL L-TYROSINE; ADENOSINE; GLYCERIN; BUTYLATED HYDROXYTOLUENE; PROPYLENE GLYCOL; LEVOMENOL; HEXYLENE GLYCOL; SODIUM ACRYLATE/SODIUM ACRYLOYLDIMETHYLTAURATE COPOLYMER (4000000 MW); TRIPOLYPHOSPHATE ION; COCO GLUCOSIDE; SILICON DIOXIDE

ANTI-AGING COMPLEX EMULSION BROAD SPECTRUM SPF 30

Active ingredients Purpose

Avobenzone 3.0% Sunscreen

Homosalate 8.0% Sunscreen

Octisalate 4.0% Sunscreen

Octocrylene 2.35% Sunscreen

Oxybenzone 5.0% Sunscreen

Uses

- helps prevent sunburn
- If used as directed with other sun protection measures (see Directions), decreases the risk of skin cancer and early skin aging by the sun

Keep out of reach of children. If swallowed, get medical help or contact a Poison Control Center right away.

Warnings

For external use only

Do not use on damaged or broken skin

When using this product keep out of eye. Rinse with water to remove.

Stop use and ask a doctor if rush occurs.

Directions

- For sunscreen use:
- apply liberally and evenly 15 minutes before sun exposure
- use a water resistant sunscreen if swimming or sweating
- reapply at least every 2 hours
- children under 6 months: Ask a doctor
- Sun Protection Measures. Spending time in the sun increases your risk of skin cancer and early skin aging. To decrease this risk, regularly use a sunscreen with a Broad Spectrum SPF value of 15 or higher and other sun protection measures including:
- limit time in the sun, especially from 10 a.m. - 2 p.m.
- wear long-sleeved shirts, pants, hats, and sunglasses
- children under 6 months: Ask a doctor
- Apply to cleansed and toned skin prior to sun exposure.

INACTIVE INGREDIENT

Inactive ingredients: Aqua/Water/Eau, Glycerin, Ethoxydiglycol, Butylene Glycol, Alcohol Denat., Cyclopentasiloxane, Glycereth-26, Isostearyl Neopentanoate, Nylon-12, Glyceryl Stearate, Bis-Ethylhexyl Hydroxydimethoxy Benzylmalonate, Isononyl Isononanoate, Phenoxyethanol, Ammonium Acryloyldimethyltaurate/VP Copolymer, Polymethyl Methacrylate, Hydrolyzed Malt Extract, Sodium Acrylate/Sodium Acryloyldimethyl Taurate Copolymer, Polyisobutene, Hydrogenated Lecithin, PEG-100 Stearate, Caprylyl Glycol, Mica (CI 77019), Coco-Glucoside, Ethylhexylglycerin, Tetrasodium EDTA, Xanthan Gum, Coconut Alcohol, BHT, Bisabolol, Hexylene Glycol, Propylene Glycol, Caprylyl/Capryl Glucoside, Opuntia Ficus-Indica Stem Extract, Hydroxypropyl Cyclodextrin, Acetyl Tyrosine, Phospholipids, Panax Ginseng Root Extract, Camellia Sinensis Leaf Extract, Proline, Silica, Adenosine Triphosphate, Hydrolyzed Vegetable Protein, Acetyl Octapeptide-3, Equisetum Arvense Extract, Acetylarginyltryptophyl Diphenylglycine, Ascorbyl Palmitate, Retinyl Palmitate, Palmitoyl Tripeptide-38, Tocopheryl Acetate.

Questions or comments?

1-800-421-2060 9:00 a.m. - 5:00 p.m. PST

Other information

- protect this product from excessive heat and direct sun

PACKAGE LABEL

ANTI-AGING COMPLEX EMULSION

BROAD SPECTRUM SPF 30

MERLE NORMAN

31 g NET WT. 1.1 OZ.